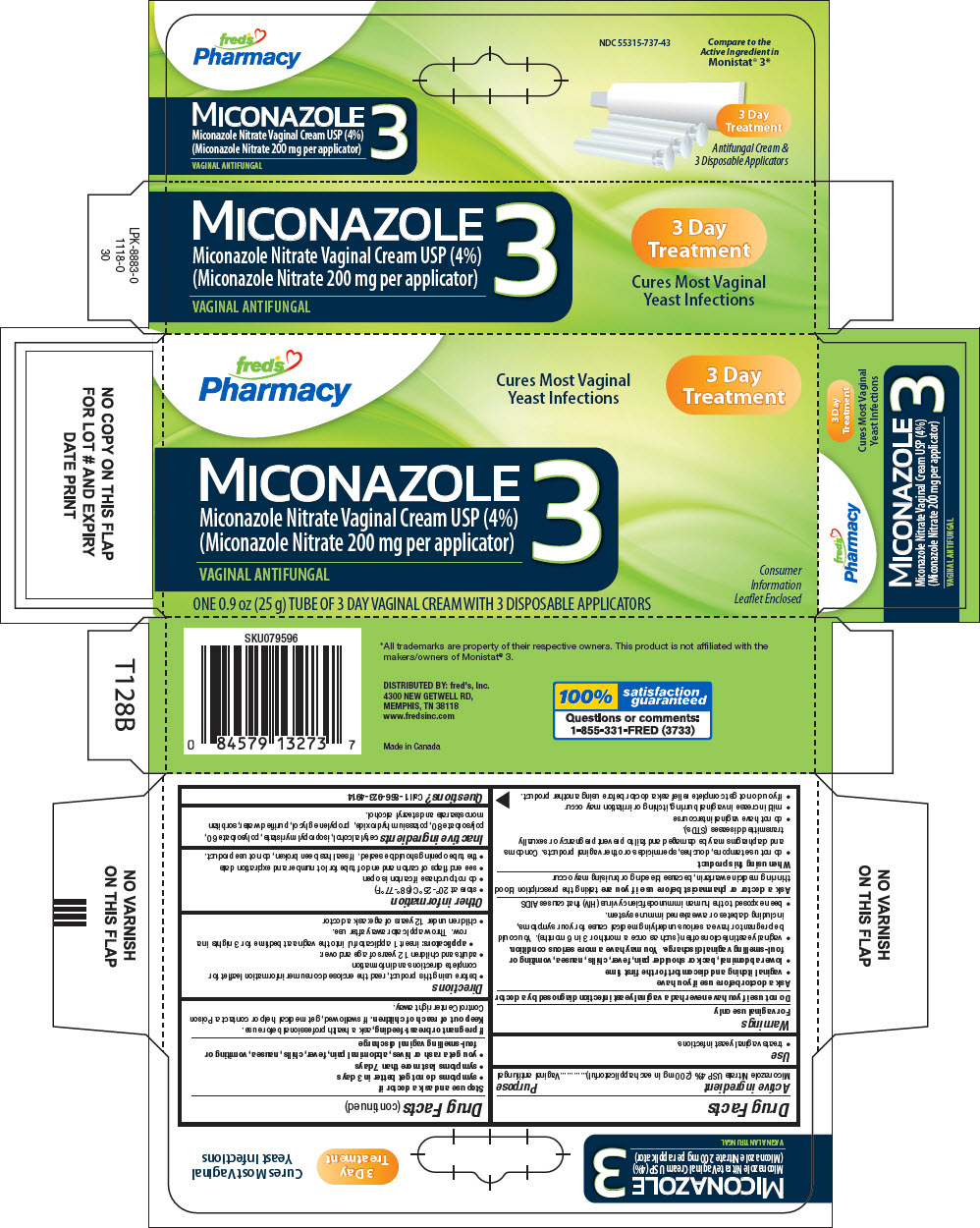 DRUG LABEL: Freds 
NDC: 55315-737 | Form: CREAM
Manufacturer: FRED'S, INC.
Category: otc | Type: HUMAN OTC DRUG LABEL
Date: 20190102

ACTIVE INGREDIENTS: Miconazole Nitrate 40 mg/1 g
INACTIVE INGREDIENTS: cetyl alcohol; isopropyl myristate; polysorbate 60; polysorbate 80; potassium hydroxide; propylene glycol; water; sorbitan monostearate; stearyl alcohol

Fred's
Miconazole 3

Drug Facts

Active ingredient

Miconazole Nitrate USP 4% (200 mg in each applicatorful)

Purpose

Vaginal antifungal

Use

- treats vaginal yeast infections

Warnings

For vaginal use only

Do not use if you have never had a vaginal yeast infection diagnosed by a doctor

Ask a doctor before use if you have

- vaginal itching and discomfort for the first time
- lower abdominal, back or shoulder pain, fever, chills, nausea, vomiting or foul-smelling vaginal discharge. You may have a more serious condition.
- vaginal yeast infections often (such as once a month or 3 in 6 months). You could be pregnant or have a serious underlying medical cause for your symptoms, including diabetes or a weakened immune system.
- been exposed to the human immunodeficiency virus (HIV) that causes AIDS

Ask a doctor or pharmacist before use if you are taking the prescription blood thinning medicine warfarin, because bleeding or bruising may occur

When using this product

- do not use tampons, douches, spermicides or other vaginal products. Condoms and diaphragms may be damaged and fail to prevent pregnancy or sexually transmitted diseases (STDs).
- do not have vaginal intercourse
- mild increase in vaginal burning, itching or irritation may occur
- if you do not get complete relief ask a doctor before using another product.

Stop use and ask a doctor if

- symptoms do not get better in 3 days
- symptoms last more than 7 days
- you get a rash or hives, abdominal pain, fever, chills, nausea, vomiting or foul-smelling vaginal discharge

PREGNANCY OR BREAST FEEDING

If pregnant or breast-feeding, ask a health professional before use.

Keep out of reach of children. If swallowed, get medical help or contact a Poison Control Center right away.

Directions

- before using this product, read the enclosed consumer information leaflet for complete directions and information
- adults and children 12 years of age and over:
  - applicators: insert 1 applicatorful into the vagina at bedtime for 3 nights in a row. Throw applicator away after use.
- children under 12 years of age: ask a doctor

Other information

- store at 20°-25°C (68°-77°F)
- do not purchase if carton is open
- see end flaps of carton and end of tube for lot number and expiration date
- the tube opening should be sealed. If seal has been broken, do not use product.

Inactive ingredients

cetyl alcohol, isopropyl myristate, polysorbate 60, polysorbate 80, potassium hydroxide, propylene glycol, purified water, sorbitan monostearate and stearyl alcohol.

Questions?

Call 1-866-923-4914

DISTRIBUTED BY: fred's, Inc.
4300 NEW GETWELL RD,
MEMPHIS, TN 38118

PRINCIPAL DISPLAY PANEL - 25 g Tube Carton

fred's
Pharmacy

Cures Most Vaginal
Yeast Infections

3 Day
Treatment

MICONAZOLE
3
Miconazole Nitrate Vaginal Cream USP (4%)
(Miconazole Nitrate 200 mg per applicator)

VAGINAL ANTIFUNGAL

ONE 0.9 oz (25 g) TUBE OF 3 DAY VAGINAL CREAM WITH 3 DISPOSABLE APPLICATORS

Consumer
Information
Leaflet Enclosed